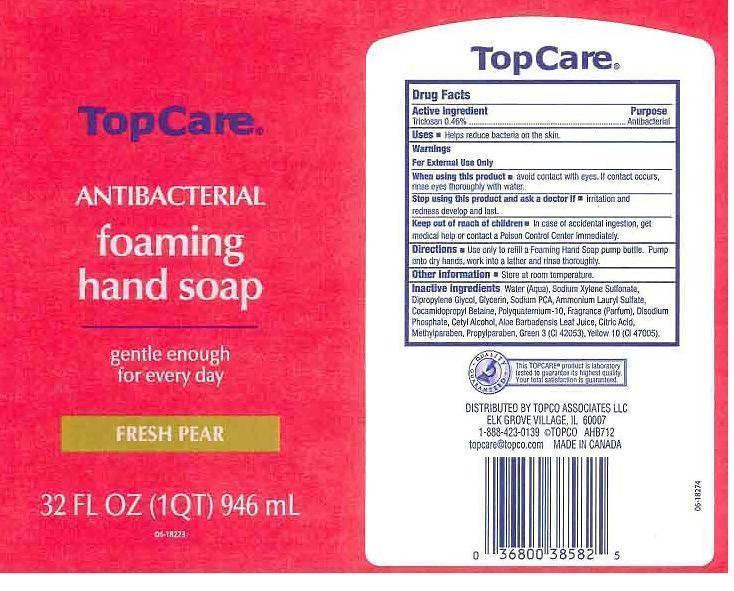 DRUG LABEL: TOPCARE
NDC: 36800-195 | Form: LIQUID
Manufacturer: TOPCO ASSOCIATES LLC
Category: otc | Type: HUMAN OTC DRUG LABEL
Date: 20121026

ACTIVE INGREDIENTS: TRICLOSAN 4.6 mg/1 mL
INACTIVE INGREDIENTS: WATER; SODIUM XYLENESULFONATE; DIPROPYLENE GLYCOL; GLYCERIN; SODIUM PYRROLIDONE CARBOXYLATE; AMMONIUM LAURYL SULFATE; COCAMIDOPROPYL BETAINE; POLYQUATERNIUM-10 (400 CPS AT 2%); SODIUM PHOSPHATE, DIBASIC, ANHYDROUS; CETYL ALCOHOL; ALOE VERA LEAF; CITRIC ACID MONOHYDRATE; METHYLPARABEN; PROPYLPARABEN; FD&C GREEN NO. 3; D&C YELLOW NO. 10

DRUG FACTS

ACTIVE INGREDIENT

TRICLOSAN 0.46%

PURPOSE

ANTIBACTERIAL

USES

HELPS REDUCE BACTERIA ON THE SKIN.

WARNINGS

FOR EXTERNAL USE ONLY.

WHEN USING THIS PRODUCT

AVOID CONTACT WITH EYES. IF CONTACT OCCURS, RINSE EYES THOROUGHLY WITH WATER.

STOP USING THIS PRODUCT AND ASK A DOCTOR IF

IRRITATION AND REDNESS DEVELOP AND LAST.

KEEP OUT OF REACH OF CHILDREN

IN CASE OF ACCIDENTAL INGESTION, GET MEDICAL HELP OR CONTACT A POISON CONTROL CENTER IMMEDIATELY.

DIRECTIONS

USE ONLY TO REFILL A FOAMING HAND SOAP PUMP BOTTLE. PUMP ONTO DRY HANDS, WORK INTO A LATHER AND RINSE THOROUGHLY.

OTHER INFORMATION

STORE AT ROOM TEMPERATURE.

INACTIVE INGREDIENTS

WATER (AQUA), SODIUM XYLENESULFONATE, DIPROPYLENE GLYCOL, GLYCERIN, SODIUM PCA, AMMONIUM LAURYL SULFATE, COCAMIDOPROPYL BETAINE, POLYQUATERNIUM-10, FRAGRANCE (PARFUM), DISODIUM PHOSPHATE, CETYL ALCOHOL, ALOE BARBADENSIS LEAF JUICE, CITRIC ACID, METHYLPARABEN, PROPYLPARABEN, GREEN 3 (CI 42053), YELLOW 10 (CI 47005).